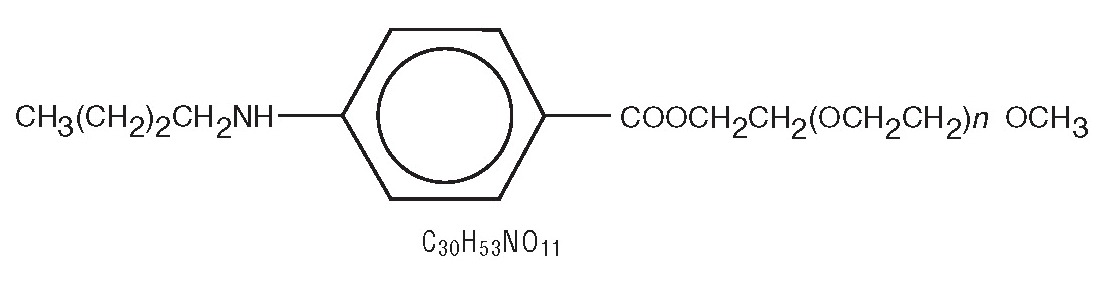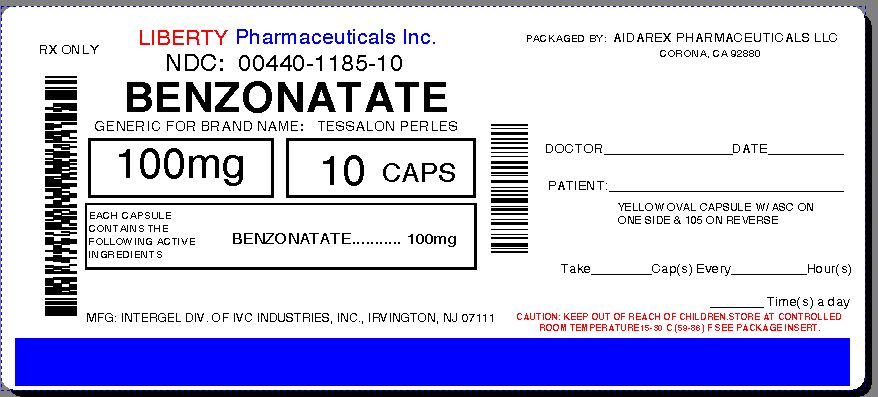 DRUG LABEL: benzonatate
NDC: 0440-1185 | Form: CAPSULE
Manufacturer: Liberty Pharmaceuticals, Inc.
Category: prescription | Type: HUMAN PRESCRIPTION DRUG LABEL
Date: 20130822

ACTIVE INGREDIENTS: BENZONATATE 100 mg/1 1
INACTIVE INGREDIENTS: D&C YELLOW NO. 10; GELATIN; GLYCERIN; WATER; METHYLPARABEN; PROPYLPARABEN; TITANIUM DIOXIDE

BENZONATATE - INTERGEL

DESCRIPTION

Benzonatate, a non-narcotic oral antitussive agent, is 2, 5, 8, 11, 14, 17, 20, 23, 26-nonaoxaoctacosan-28-yl p-(butylamino) benzoate; with a molecular weight of 603.7.

Each soft gelatin capsule, for oral administration, contains 100 mg or 200 mg of benzonatate USP.
Benzonatate Capsules, USP also contain the following inactive ingredients: D&C Yellow # 10, gelatin, glycerin, purified water, methylparaben, propylparaben and titanium dioxide.

CLINICAL PHARMACOLOGY

Benzonatate acts peripherally by anesthetizing the stretch receptors located in the respiratory passages, lungs, and pleura by dampening their activity and thereby reducing the cough reflex at its source. It begins to act within 15 to 20 minutes and its effect lasts for 3 to 8 hours. Benzonatate has no inhibitory effect on the respiratory center in recommended dosage.

INDICATIONS AND USAGE

Benzonatate is indicated for the symptomatic relief of cough.

CONTRAINDICATIONS

Hypersensitivity to benzonatate or related compounds.

WARNINGS

Severe hypersensitivity reactions (including bronchospasm, laryngospasm and cardiovascular collapse) have been reported which are possibly related to local anesthesia from sucking or chewing the capsule instead of swallowing it. Severe reactions have required intervention with vasopressor agents and supportive measures.

Isolated instances of bizarre behavior, including mental confusion and visual hallucinations, have also been reported in patients taking benzonatate in combination with other prescribed drugs.

PRECAUTIONS

Benzonatate is chemically related to anesthetic agents of the para-aminobenzoic acid class (e.g. procaine; tetracaine) and has been associated with adverse CNS effects possibly related to a prior sensitivity to related agents or interaction with concomitant medication.

Information for patients:

Release of benzonatate from the capsule in the mouth can produce a temporary local anesthesia of the oral mucosa and choking could occur. Therefore, the capsules should be swallowed without chewing.

Usage in Pregnancy:

Pregnancy Category C. Animal reproduction studies have not been conducted with benzonatate. It is also not known whether benzonatate can cause fetal harm when administered to a pregnant woman or can affect reproduction capacity. Benzonatate should be given to a pregnant woman only if clearly needed.

Nursing Mothers:

It is not known whether this drug is excreted in human milk. Because many drugs are excreted in human milk caution should be exercised when benzonatate is administered to a nursing woman.

Carcinogenesis, mutagenesis, impairment of fertility:

Carcinogenicity, mutagenicity, and reproduction studies have not been conducted with benzonatate.

Pediatric Use:

Safety and effectiveness in children below the age of 10 have not been established.

ADVERSE REACTIONS

Potential Adverse Reactions to benzonatate may include:

Hypersensitivity reactions including bronchospasm, laryngospasm, cardiovascular collapse possibly related to local anesthesia from chewing or sucking the capsule.

CNS: sedation; headache; dizziness; mental confusion; visual hallucinations.

GI: constipation; nausea; GI upset.

Dermatologic: pruritus; skin eruptions.

Other: nasal congestion; sensation of burning in the eyes; vague “chilly” sensation; numbness of the chest; hypersensitivity.

Rare instances of deliberate or accidental overdose have resulted in death.

OVERDOSAGE

Overdose may result in death.

The drug is chemically related to tetracaine and other topical anesthetics and shares various aspects of their pharmacology and toxicology. Drugs of this type are generally well absorbed after ingestion.

Signs and Symptoms:
If capsules are chewed or dissolved in the mouth, oropharyngeal anesthesia will develop rapidly. CNS stimulation may cause restlessness and tremors which may proceed to clonic convulsions followed by profound CNS depression.

Treatment:
Evacuate gastric contents and administer copious amounts of activated charcoal slurry. Even in the conscious patient, cough and gag reflexes may be so depressed as to necessitate special attention to protection against aspiration of gastric contents and orally administered materials. Convulsions should be treated with a short-acting barbiturate given intravenously and carefully titrated for the smallest effective dosage. Intensive support of respiration and cardiovascular - renal function is an essential feature of the treatment of severe intoxication from overdosage.

Do not use CNS stimulants.

DOSAGE AND ADMINISTRATION

Adults and Children over 10 years of age: Usual dose is one 100 mg or 200 mg capsule t.i.d. as required. If necessary, up to 600 mg daily may be given.

HOW SUPPLIED

Benzonatate Capsules USP, 100 mg: Yellow soft gelatin capsules, imprinted “ASC” on one side and “105” on the other side, available in bottles of 10’s (NDC 00440-1185-10).

Store at controlled room temperature 20º - 25ºC (68º - 77ºF) [See USP].

API-01, 5/07

Mfd by
Intergel Division of IVC Industries, Inc.
Irvington, NJ 07111

Repackaged By:
Aidarex Pharmaceuticals, LLC
Corona, CA 92880